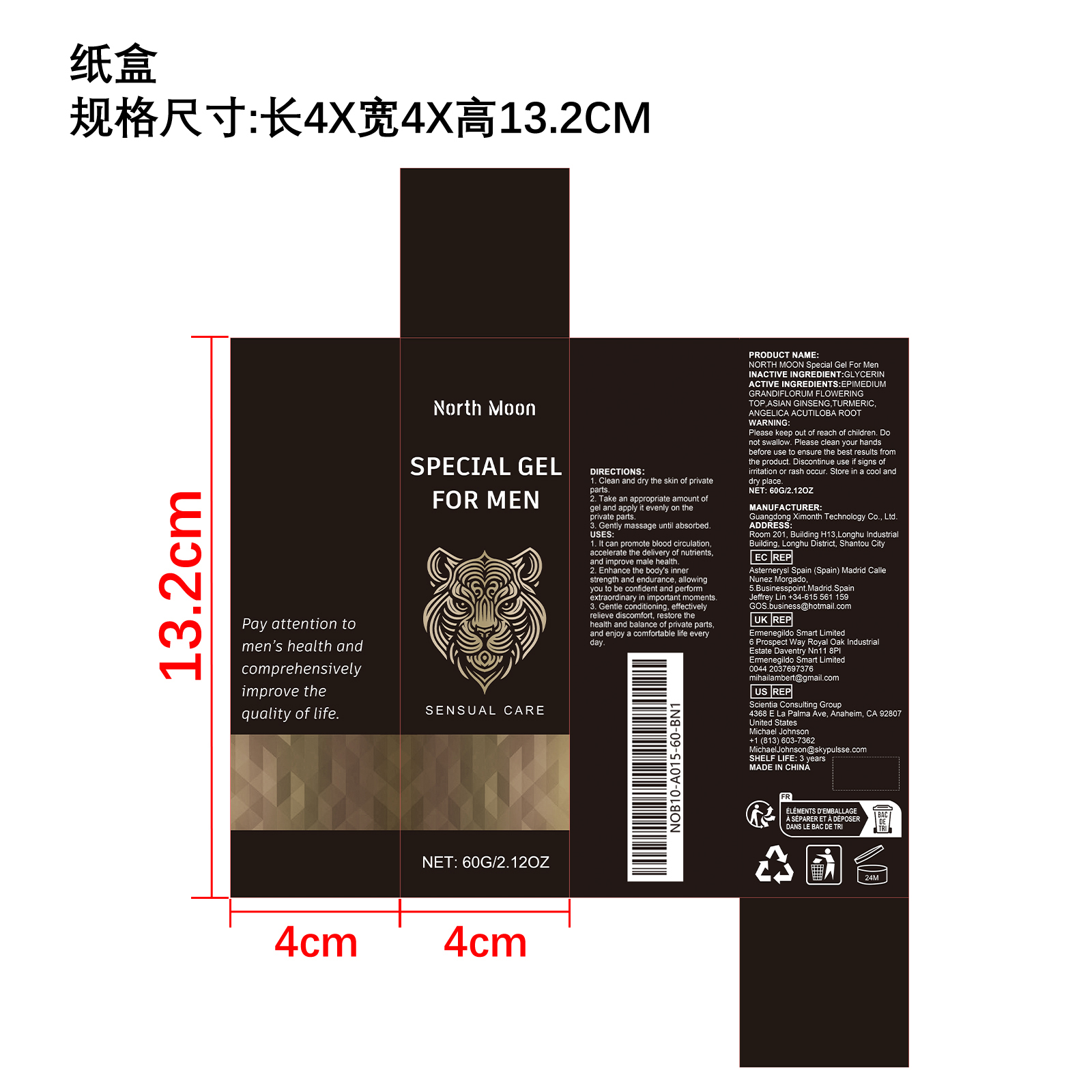 DRUG LABEL: NORTH MOON Special Gel For Men
NDC: 84660-043 | Form: GEL
Manufacturer: Guangdong Ximonth Technology Co., Ltd.
Category: otc | Type: HUMAN OTC DRUG LABEL
Date: 20241016

ACTIVE INGREDIENTS: ASIAN GINSENG 18 g/60 g; TURMERIC 9 g/60 g; ANGELICA ACUTILOBA ROOT 9 g/60 g; EPIMEDIUM GRANDIFLORUM FLOWERING TOP 6 g/60 g
INACTIVE INGREDIENTS: GLYCERIN 18 g/60 g

ACTIVE INGREDIENT(S)

EPIMEDIUM GRANDIFLORUM FLOWERING TOP,ASIAN GINSENG,TURMERIC,ANGELICA ACUTILOBA ROOT

Purpose

It can promote blood circulation, accelerate the delivery of nutrients, and improve male health

USE

1. Clean and dry the skin of private parts.

2. Take an appropriate amount of gel and apply it evenly on the private parts.

3. Gently massage until absorbed.

WARNINGS

Please keep out of reach of children. Do not swallow. Please clean your hands before use to ensure the best results from the product. Discontinue use if signs of irritation or rash occur. Store in a cool and dry place.

Do not use

Discontinue use if signs of irritation or rash occur

STOP USE

Discontinue use if signs of irritation or rash occur

KEEP OUT OF REACH OF CHILDREN

Please keep out of reach of children. Do not swallow

STORAGE AND HANDLING

Store in a cool and dry place.

INACTIVE INGREDIENT

GLYCERIN